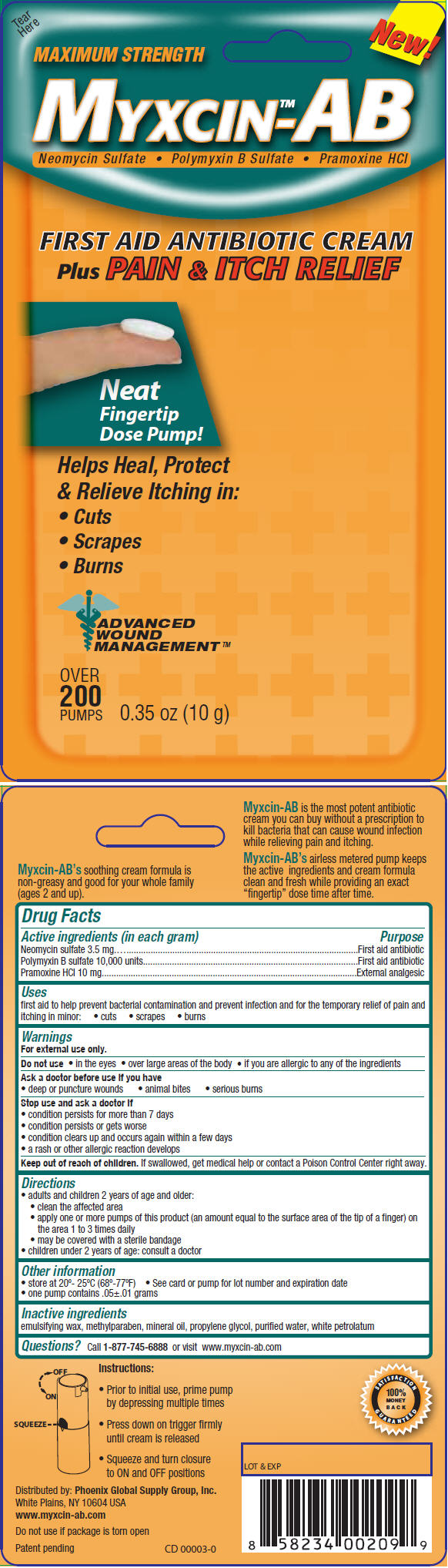 DRUG LABEL: ANTIBIOTIC PLUS PAIN RELIEF
NDC: 52426-220 | Form: CREAM
Manufacturer: Phoenix Global Supply Group, Inc.
Category: otc | Type: HUMAN OTC DRUG LABEL
Date: 20110602

ACTIVE INGREDIENTS: Neomycin Sulfate 3.5 mg/1 g; Polymyxin B Sulfate 10000 [iU]/1 g; Pramoxine Hydrochloride 10 mg/1 g
INACTIVE INGREDIENTS: methylparaben; mineral oil; propylene glycol; water; petrolatum

MYXCIN™-AB

Drug Facts

ACTIVE INGREDIENT

Active ingredients (in each gram) | Purpose
Neomycin sulfate 3.5 mg | First aid antibiotic
Polymyxin B sulfate 10,000 units | First aid antibiotic
Pramoxine HCl 10 mg | External analgesic

Uses

first aid to help prevent bacterial contamination and prevent infection and for the temporary relief of pain and itching in minor:

- cuts
- scrapes
- burns

Warnings

For external use only.

Do not use

- in the eyes
- over large areas of the body
- if you are allergic to any of the ingredients

Ask a doctor before use if you have

- deep or puncture wounds
- animal bites
- serious burns

Stop use and ask a doctor if

- condition persists for more than 7 days
- condition persists or gets worse
- condition clears up and occurs again within a few days
- a rash or other allergic reaction develops

Keep out of reach of children. If swallowed, get medical help or contact a Poison Control Center right away.

Directions

- adults and children 2 years of age and older:
  - clean the affected area
  - apply one or more pumps of this product (an amount equal to the surface area of the tip of a finger) on the area 1 to 3 times daily
  - may be covered with a sterile bandage
- children under 2 years of age: consult a doctor

Other information

- store at 20°- 25°C (68°-77°F)
- See card or pump for lot number and expiration date
- one pump contains .05±.01 grams

Inactive ingredients

emulsifying wax, methylparaben, mineral oil, propylene glycol, purified water, white petrolatum

Questions?

Call 1-877-745-6888 or visit www.myxcin-ab.com

PRINCIPAL DISPLAY PANEL - 10 g Blister Pack

New!

MAXIMUM STRENGTH

MYXCIN™-AB

Neomycin Sulfate • Polymyxin B Sulfate • Pramoxine HCl

FIRST AID ANTIBIOTIC CREAM
Plus PAIN & ITCH RELIEF

Neat
Fingertip
Dose Pump!

Helps Heal, Protect
& Relieve Itching in:

- Cuts
- Scrapes
- Burns

ADVANCED
WOUND
MANAGEMENT ™

OVER
200
PUMPS

0.35 oz (10 g)